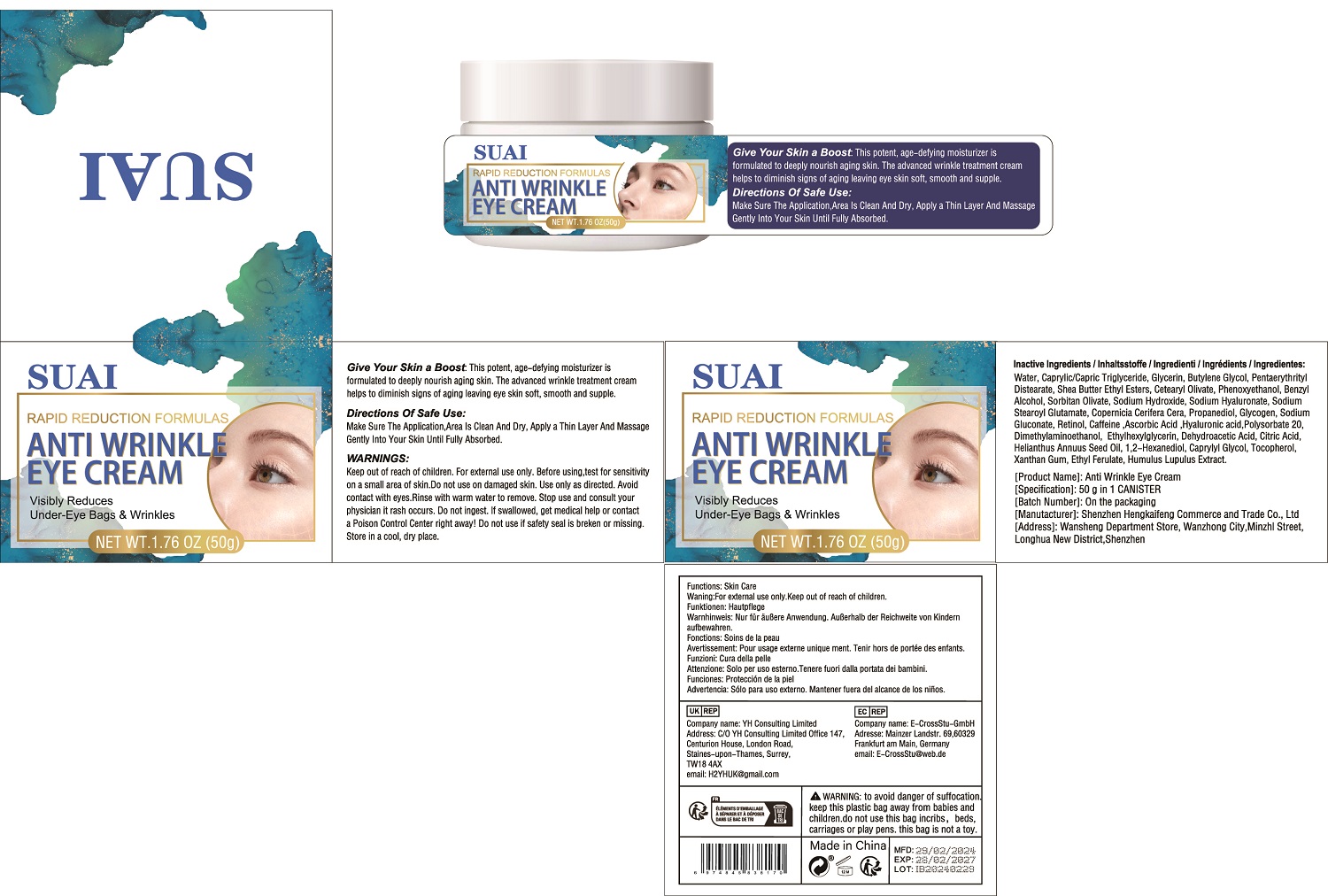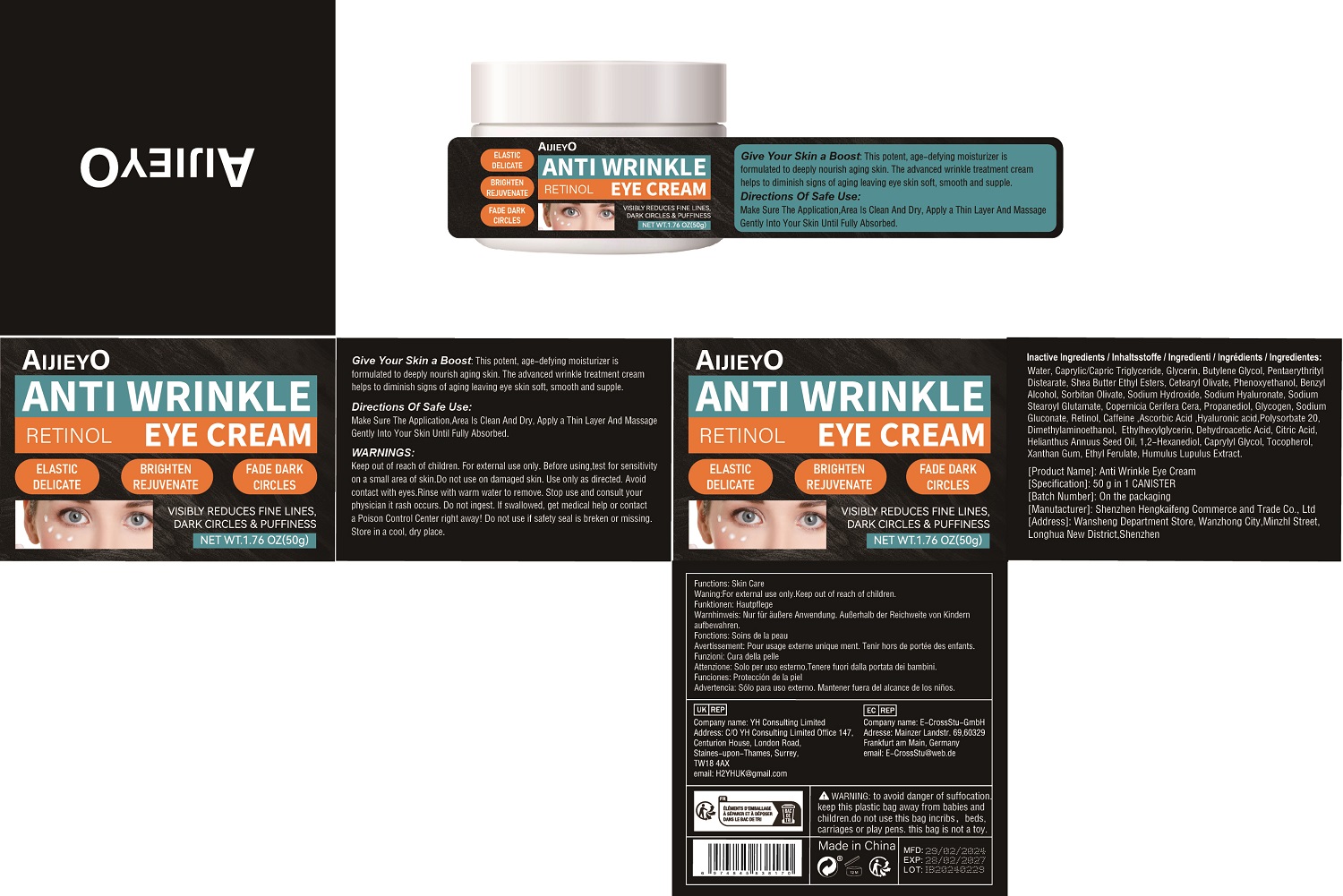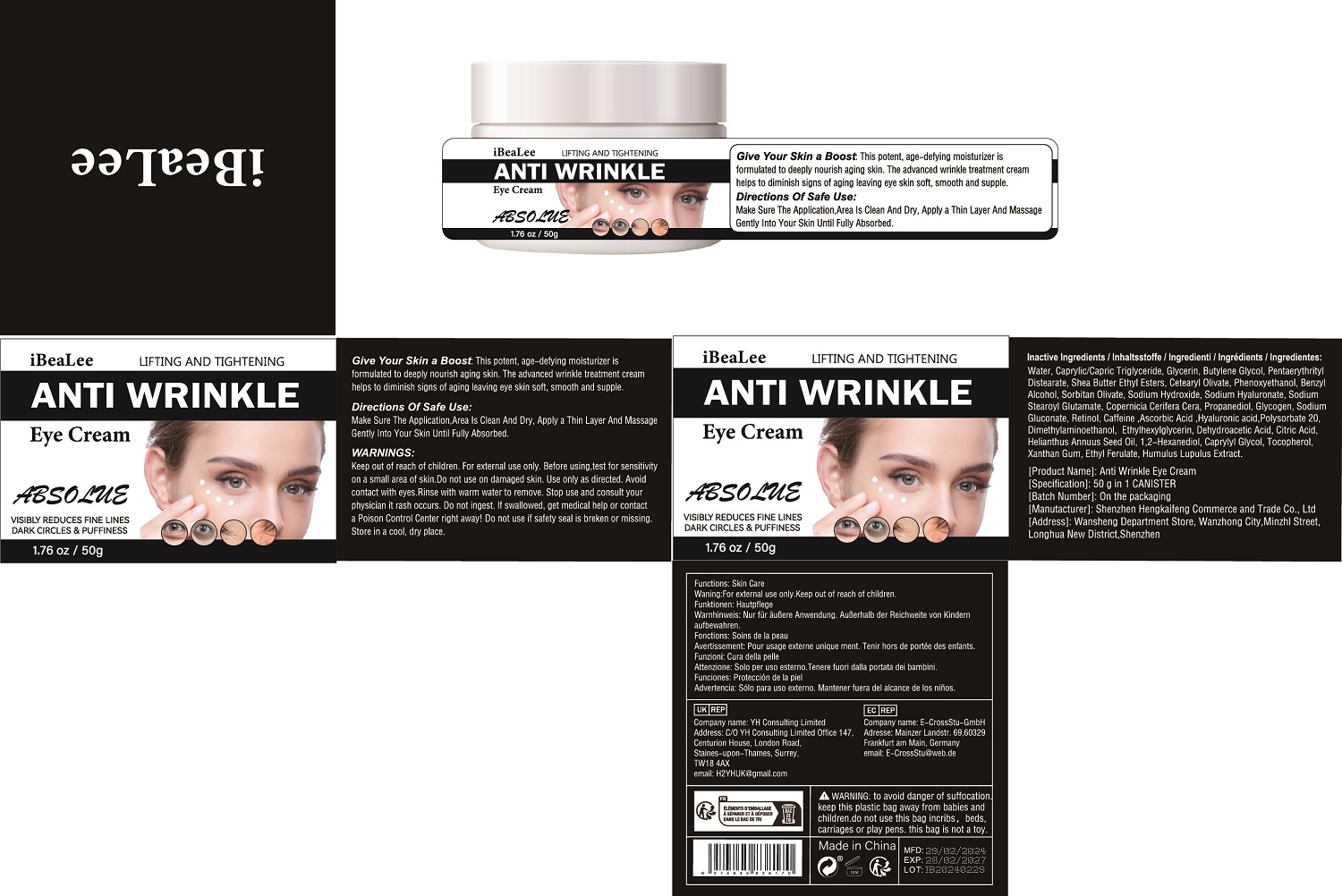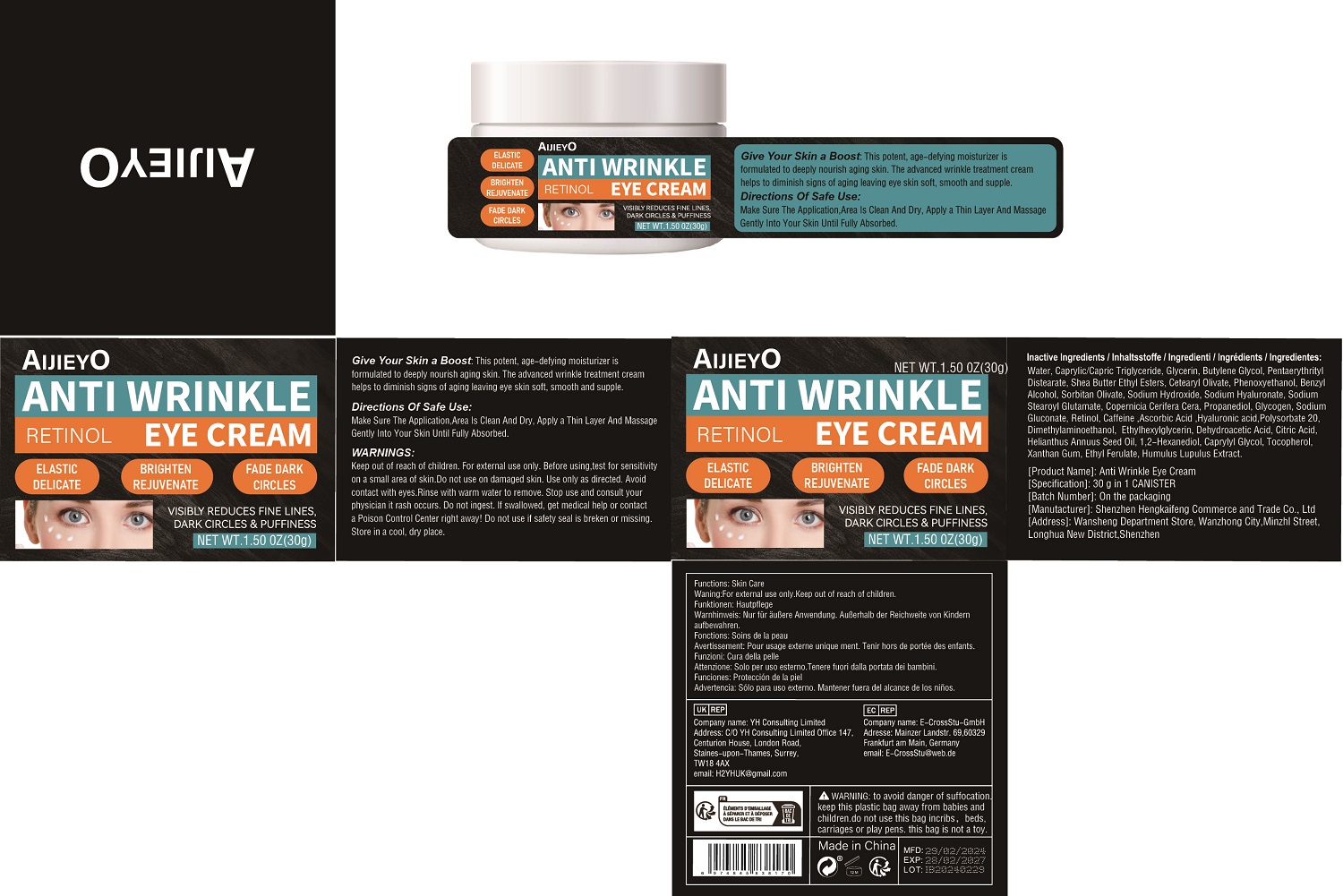 DRUG LABEL: Anti Wrinkle Eye Cream
NDC: 84117-009 | Form: CREAM
Manufacturer: Shenzhen Hengkaifeng Commerce and Trade Co., Ltd
Category: otc | Type: HUMAN OTC DRUG LABEL
Date: 20240511

ACTIVE INGREDIENTS: RETINOL 1 g/100 g
INACTIVE INGREDIENTS: ETHYLHEXYLGLYCERIN; SUNFLOWER OIL; 1,2-HEXANEDIOL; TOCOPHEROL; BUTYLENE GLYCOL; CETEARYL OLIVATE; PHENOXYETHANOL; HYALURONIC ACID; DEHYDROACETIC ACID; XANTHAN GUM; PROPANEDIOL; WATER; MEDIUM-CHAIN TRIGLYCERIDES; CAFFEINE; CITRIC ACID MONOHYDRATE; ETHYL FERULATE; BENZYL ALCOHOL; ASCORBIC ACID; POLYSORBATE 20; PENTAERYTHRITYL DISTEARATE; SHEA BUTTER ETHYL ESTERS; CAPRYLYL GLYCOL; HOPS; SODIUM GLUCONATE; SORBITAN OLIVATE; PEG-9 DIGLYCIDYL ETHER/SODIUM HYALURONATE CROSSPOLYMER; GLYCERIN; SODIUM HYDROXIDE; DEANOL; SODIUM STEAROYL GLUTAMATE; GLYCOGEN

ACTIVE INGREDIENT

Retinol 1%

Purpose

anti wrinkle

Use

Give Your Skin a Boost: This potent, age-defying moisturizer is
formulated to deeply nourish aging skin. The advanced wrinkle treatment cream
helps to diminish signs of aging leaving eye skin soft, smooth and supple.

Warnings

Keep out of reach of children. For external use only. Before using,test for sensitivity
on a small area of skin.Do not use on damaged skin. Use only as directed. Avoid
contact with eyes.Rinse with warm water to remove. Stop use and consult your
physician it rash occurs. Do not ingest. lf swallowed, get medical help or contact
a Poison Control Center right away! Do not use if safety seal is breken or missing.
Store in a cool, dry place.

Keep Out Of Reach Of Children

Directions Of Safe Use:

Make Sure The Application,Area Is Clean And Dry, Apply a Thin Layer And Massage
Gently Into Your Skin Until Fully Absorbed.

Inactive ingredients

Water, Caprylic/Capric Triglyceride, Glycerin, Butylene Glycol, Pentaerythrityl
Distearate, Shea Butter Ethyl Esters, Cetearyl Olivate, Phenoxyethanol, Benzyl
Alcohol, Sorbitan Olivate, Sodium Hydroxide, Sodium Hyaluronate, Sodium
Stearoyl Glutamate, Copernicia Cerifera Cera, Propanediol, Glycogen, Sodium
Gluconate, Caffeine ,Ascorbic Acid ,Hyaluronic acid,Polysorbate 20,
Dimethylaminoethanol, Ethylhexylglycerin, Dehydroacetic Acid, Citric Acid,
Helianthus Annuus Seed Oil, 1,2-Hexanediol, Caprylyl Glycol, Tocopherol,
Xanthan Gum, Ethyl Ferulate, Humulus Lupulus Extract.